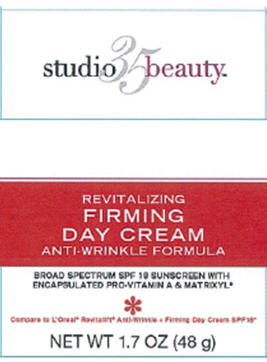 DRUG LABEL: Walgreens Advanced Anti-Wrinkle and Firming Day Cream Broad Spectrum SPF18 Sunscreen
NDC: 0363-0815 | Form: CREAM
Manufacturer: Walgreen Company
Category: otc | Type: HUMAN OTC DRUG LABEL
Date: 20140110

ACTIVE INGREDIENTS: AVOBENZONE 2 g/100 g; OCTISALATE 5 g/100 g; OCTOCRYLENE 5 g/100 g
INACTIVE INGREDIENTS: WATER; CYCLOMETHICONE 6; GLYCERIN; TITANIUM DIOXIDE; GLYCERYL MONOSTEARATE; PEG-100 STEARATE; ROYAL JELLY; MYRISTYL MYRISTATE; STEARIC ACID; PALMITIC ACID; POLYGLYCERYL-10 STEARATE; DOCOSANOL; SODIUM STEAROYL LACTYLATE; .ALPHA.-TOCOPHEROL ACETATE; BUTYLENE GLYCOL; CARBOMER COPOLYMER TYPE A (ALLYL PENTAERYTHRITOL CROSSLINKED); POLYSORBATE 20; PALMITOYL OLIGOPEPTIDE; PALMITOYL TETRAPEPTIDE-7; PROPYLENE GLYCOL; DIAZOLIDINYL UREA; METHYLPARABEN; PROPYLPARABEN; CETYL ALCOHOL; STEARYL ALCOHOL; SOY PROTEIN; DIPALMITOYL HYDROXYPROLINE; TROLAMINE; GLYCINE MAX WHOLE; XANTHAN GUM; VITAMIN A PALMITATE; PHENOXYETHANOL; PEG-20 STEARATE; POTASSIUM SORBATE; SODIUM BENZOATE; PHENYLETHYL ALCOHOL; ALCOHOL; CHLORPHENESIN

studio 35 beauty™ Revitalizing Firming Day Cream Anti-Wrinkle Formula

Active ingredient

Avobenzone 2.0%
Octisalate 5.0%
Octocrylene 5.0%

Purpose

Sunscreen

Uses

- helps prevent sunburn
- If used as directed with other sun protection measures (see Directions), decreases the risk of skin cancer and early skin aging caused by the sun

Warnings

For external use only.

When using this product

- keep out of eyes. Rinse with water to remove.

Stop use and ask a doctor

- if rash occurs.

Skin Cancer/Skin Aging Alert:

Spending time in the sun increases your risk of skin cancer and early skin aging. This product has been shown only to help prevent sunburn, not skin cancer or early skin aging.

Keep Out of Reach of Children.

If swallowed, get medical help or contact a Poison Control Center right away.

Directions

- Apply liberally 15 minutes before sun exposure.
- Children under 6 months of age: ask a doctor
- Sun Protection Measures: Spending time in the sun increases your risk of skin cancer and early skin aging. To decrease this risk, regularly use a sunscreen with a Broad Spectrum SPF value of 15 or higher and other sun protection measures including:
  - limit time in the sun, especially from 10 a.m. - 2 p.m.
  - wear long-sleeved shirts, pants, hats and sunglasses

Other Information

- protect the product in this container from excessive heat and direct sun

Inactive ingredients

water, cyclohexasiloxane, glycerin, titanium dioxide, glyceryl stearate,PEG-100 stearate, beeswax, myristyl myristate, stearic acid, palmitic acid, polyglyceryl-10 pentastearate, behenyl alcohol, sodium steroyl lactylate, tocopheryl acetate (vitamin E), butylene glycol, acrylates copolymer,polysorbate 20, palmitoyl oligopeptide, palmitoyl tetrapeptide-7, propylene glycol, diazolidinyl urea, methylparaben, propylparaben, cetyl alcohol, stearyl alcohol, hydrolyzed soy protein, dipalmitoyl hydroxyproline, fragrance, triethanolamine, glycine soja (soybean) protein, xanthan gum, retinyl palmitate (vitamin A), phenoxyethanol, PEG-20 stearate, potassium sorbate, sodium benzoate, phenethyl alcohol, alcohol denat., chlorphenesin.

Package/Label Principal Display Panel

Jar Label

studio 35 beauty™ Revitalizing Firming Day Cream Anti-Wrinkle Formula
Broad Spectrum SPF 18 Sunscreen With Encapsulated Pro-Vitamin A & Matrixyl®

Compare to L'Oreal® Revitalift® Anti-Wrinkle + Firming Day Cream SPF18

Net Wt 1.7 Oz (48 g)

Distributed by: Walgreen Co.
200 Wilmot Rd., Deerfield, IL 60015
100% Satisfaction Guaranteed

walgreens.com ©2012 Walgreen Co.

Manufactured in Israel